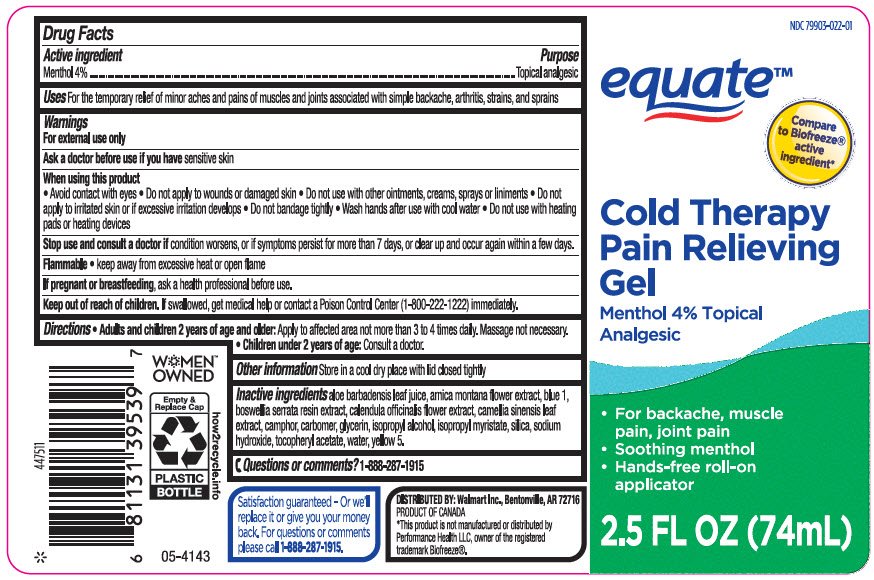 DRUG LABEL: Equate Cold Therapy Pain Relieving Roll-on
NDC: 79903-022 | Form: GEL
Manufacturer: Wal-Mart Stores, Inc.
Category: otc | Type: HUMAN OTC DRUG LABEL
Date: 20241118

ACTIVE INGREDIENTS: MENTHOL, UNSPECIFIED FORM 40 mg/1 mL
INACTIVE INGREDIENTS: ALOE VERA LEAF; Arnica Montana Flower; FD&C BLUE NO. 1; INDIAN FRANKINCENSE; Calendula Officinalis Flower; GREEN TEA LEAF; CAMPHOR (SYNTHETIC); CARBOMER HOMOPOLYMER, UNSPECIFIED TYPE; Glycerin; Isopropyl Alcohol; Isopropyl Myristate; SILICON DIOXIDE; Sodium Hydroxide; .ALPHA.-TOCOPHEROL ACETATE, DL-; Water; FD&C YELLOW NO. 5

Equate™ Cold Therapy Pain Relieving Gel Roll-on
Topical Analgesic

Drug Facts

Active ingredient

Menthol 4%

Purpose

Topical analgesic

Uses

for the temporary relief of minor aches and pains of muscles and joints associated with simple backache, arthritis, strains, bruises, and sprains

Warnings

For external use only

Ask a doctor before use if you have sensitive skin

When using this product

- Avoid contact with eyes
- Do not apply to wounds or damaged skin
- Do not use with other ointments, creams sprays or liniments
- Do not apply to irritated skin or if excessive irritation develops
- Do not bandage tightly
- Wash hands after use with cool water
- Do not use with heating pads or heating devices

Stop use and consult a doctor if condition worsens, or if symptoms persist for more than 7 days or clear up and occur again within a few days.

Flammable

- keep away from excessive heat or open flame

PREGNANCY OR BREAST FEEDING

If pregnant or breast-feeding, ask a health professional before use.

Keep out of reach of children. If swallowed, get medical help or contact a Poison Control Center (1-800-222-1222) immediately.

Directions

- Adults and children 2 years of age and older: Apply to affected area not more than 3-4 times daily.
- Children under 2 years of age: Consult a doctor.

Other information

Store in a cool dry place with lid closed tightly

Inactive ingredients

aloe barbadensis leaf juice, arnica montana flower extract, blue 1, boswellia serrata resin extract, calendula officinalis flower extract, camellia sinensis leaf extract, camphor, carbomer, glycerin, isopropyl alcohol, isopropyl myristate, silica, sodium hydroxide, tocopheryl acetate, water, yellow 5.

Questions or comments?

1-888-287-1915

DISTRIBUTED BY: Walmart Inc., Bentonville, AR 72716

PRINCIPAL DISPLAY PANEL - 74 mL Bottle Label

NDC 79903-022-01

equate™

Compare
to Biofreeze®
active
ingredient*

Cold Therapy
Pain Relieving
Gel

Menthol 4% Topical
Analgesic

- For backache, muscle
  pain, joint pain
- Soothing menthol
- Hands-free roll-on
  applicator

2.5 FL OZ (74mL)